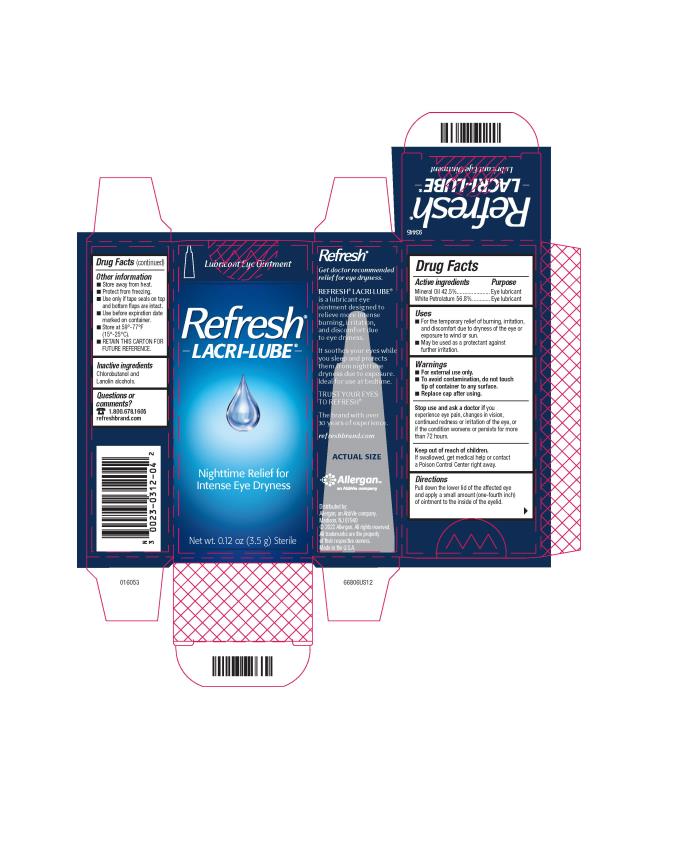 DRUG LABEL: REFRESH LACRI-LUBE
NDC: 0023-0312 | Form: OINTMENT
Manufacturer: Allergan, Inc.
Category: otc | Type: HUMAN OTC DRUG LABEL
Date: 20221201

ACTIVE INGREDIENTS: MINERAL OIL 425 mg/1 g; PETROLATUM 568 mg/1 g
INACTIVE INGREDIENTS: CHLOROBUTANOL; LANOLIN ALCOHOLS

REFRESH® LACRI-LUBE®
Drug Facts

Active ingredients

Mineral Oil 42.5%

White Petrolatum 56.8%

Purpose

Eye lubricant

Eye lubricant

Uses

- For the temporary relief of burning, irritation, and discomfort due to dryness of the eye or exposure to wind or sun.
- May be used as a protectant against further irritation.

Warnings

- For external use only.
- To avoid contamination, do not touch tip of container to any surface.
- Replace cap after using.

Stop use and ask a doctor if

you experience eye pain, changes in vision, continued redness or irritation of the eye, or if the condition worsens or persists for more than 72 hours.

Keep out of reach of children.

If swallowed, get medical help or contact a Poison Control Center right away.

Directions

Pull down the lower lid of the affected eye and apply a small amount (one-fourth inch) of ointment to the inside of the eyelid.

Other information

- Store away from heat.
- Protect from freezing.
- Use only if tape seals on top and bottom flaps are intact.
- Use before expiration date marked on container.
- Store at 59°-77°F (15°-25°C).
- RETAIN THIS CARTON FOR FUTURE REFERENCE.

Inactive ingredients

Chlorobutanol and Lanolin alcohols.

Questions or comments?

1.800.678.1605

refreshbrand.com

Principal Display Panel

NDC 0023-0312-04

Lubricant Eye Ointment

Refresh®
LACRI-LUBE®

Nighttime Relief for
Intense Eye Dryness

Net wt. 0.12 oz (3.5 g) Sterile